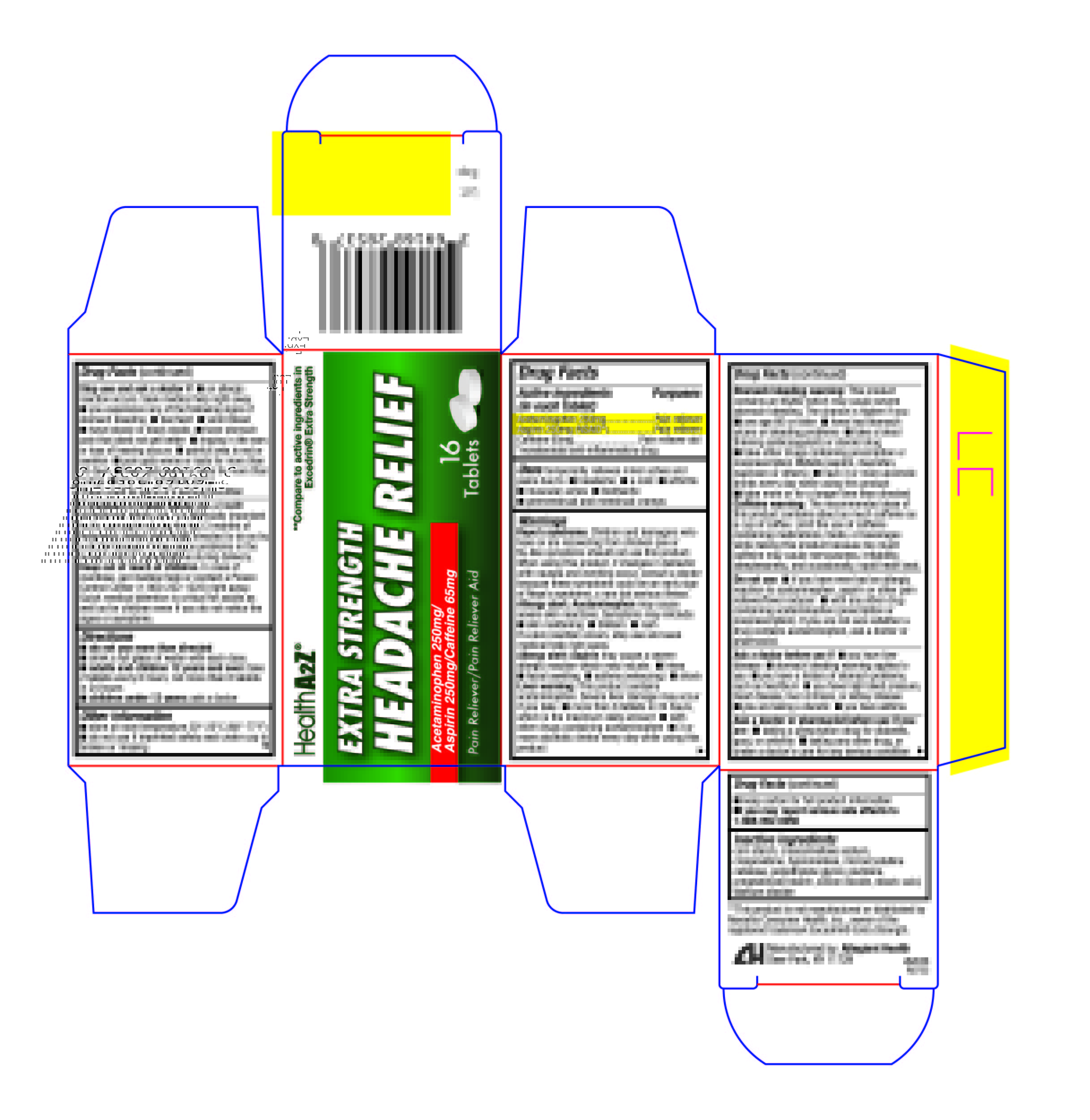 DRUG LABEL: Headache Relief
NDC: 69168-285 | Form: TABLET, FILM COATED
Manufacturer: Allegiant Health
Category: otc | Type: HUMAN OTC DRUG LABEL
Date: 20181228

ACTIVE INGREDIENTS: ACETAMINOPHEN 250 mg/1 1; ASPIRIN 250 mg/1 1; CAFFEINE 65 mg/1 1
INACTIVE INGREDIENTS: POVIDONE; PROPYLENE GLYCOL; STEARIC ACID; TITANIUM DIOXIDE; STARCH, CORN; POLYETHYLENE GLYCOL, UNSPECIFIED; SODIUM STARCH GLYCOLATE TYPE A CORN

Drug Facts

Active ingredient (in each tablet)

Acetaminophen 250 mg
Aspirin 250 mg (NSAID*)
Caffeine 65 mg

* nonsteroidal anti-inflammatory drug

Purpose

Pain reliever
Pain reliever
Pain reliever aid

Uses

temporary relief of minor aches and pains associated with ■ headache ■ common cold ■ sinusitis ■ toothache ■ muscular aches ■ arthritis ■ premenstrual and menstrual cramps

Warnings

Reye’s syndrome: Children and teenagers who have or are recovering from chicken pox or flu-like symptoms should not use this product. When using this product, if changes in behavior with nausea and vomiting occur, consult a doctor because these symptoms could be an early sign of Reye’s syndrome, a rare but serious illness.

Allergy alert: Acetaminophen may cause severe skin reactions. Symptoms may include:

- skin reddening
- blisters
- rash

If a skin reaction occurs, stop use and seek medical help right away.

Allergy alert: Aspirin may cause a severe allergic reaction which may include:

- hives
- facial swelling
- asthma (wheezing)
- shock

Liver warning: This product contains acetaminophen. Severe liver damage may occur if

- adult takes more than 8 tablets in 24 hours, which is the maximum daily amount
- taken with other drugs containing acetaminophen
- adult has 3 or more alcoholic drinks every day while using this product

Stomach bleeding warning: This product contains an NSAID, which may cause severe stomach bleeding. The chance is higher if you:

- are age 60 or older
- have had stomach ulcers or bleeding problems
- take a blood thinning (anticoagulant) or steroid drug
- take other drugs containing prescription or nonprescription NSAIDs (aspirin, ibuprofen, naproxen, or others)
- have 3 or more alcoholic drinks every day while using this product
- take more or for a longer time than directed

Caffeine warning: The recommended dose of this product contains about as much caffeine as a cup of coffee. Limit the use of caffeine-containing medications, foods, or beverages while taking this product because too much caffeine may cause nervousness, irritability, sleeplessness, and, occasionally, rapid heart beat.

Do not use

- if you have ever had an allergic reaction to acetaminophen, aspirin or any other pain reliever/fever reducer
- with any other drug containing acetaminophen (prescription or nonprescription). If you are not sure whether a drug contains acetaminophen, ask a doctor or pharmacist

Ask doctor before use if

- you have liver disease
- stomach bleeding warning applies to you
- you have a history of stomach problems, such as heartburn
- you have high blood pressure, heart disease, liver cirrhosis, or kidney disease
- you are taking a diuretic
- you have asthma

Ask a doctor or pharmacist before use if you are taking

- any other drug containing an NSAID (prescription or nonprescription)
- a blood thinning (anticoagulant) or steroid drug
- a prescription drug for diabetes, gout, or arthritis
- any other drug, or are under a doctor's care for any serious condition

Stop use and ask a doctor if

- an allergic reaction occurs. Seek medical help right away
- you feel faint, vomit blood, have bloody or black stools. These are signs of stomach bleeding.
- stomach pain or upset gets worse or lasts
- ringing in ears or loss of hearing occurs
- pain gets worse or lasts for more than 10 days
- fever gets worse or lasts for more than 3 days
- painful area is red or swollen
- new symptoms occur

If pregnant or breast-feeding

ask a health professional before use. It is especially important not to use aspirin during the last 3 months of pregnancy unless definitely directed to do so by a doctor because it may cause problems in the unborn child or complications during delivery.

Keep out of reach of children.

In case of overdose, get medical help or contact a Poison Control Center immeaditely. Prompt medical attention is critical for adults as well as for children even if you do not notice any signs or symptoms.

Directions

Do not exceed recommended dosage.

Drink a full glass of water with each dose.

Adults and children 12 years and over: take 2 tablets every 6 hours. Do not take more than 8 tablets in 24 hours.

Children under 12 years: ask a doctor

Other information

- store at 20º-25ºC (68º-77ºF)
- keep carton for full product information
- do not use if imprinted safety seal under cap is broken or missing
- you may report serious side effects to 1-888-952-0050

Inactive Ingredients

corn starch, cros- carmellose sodium, crospovidone, hypromellose, microcrystalline cellulose, polyethylene glycol, povidone, pregelatinized starch, silicon dioxide, stearic acid, titanium dioxide

Package/Label Principal Display Panel

Headache